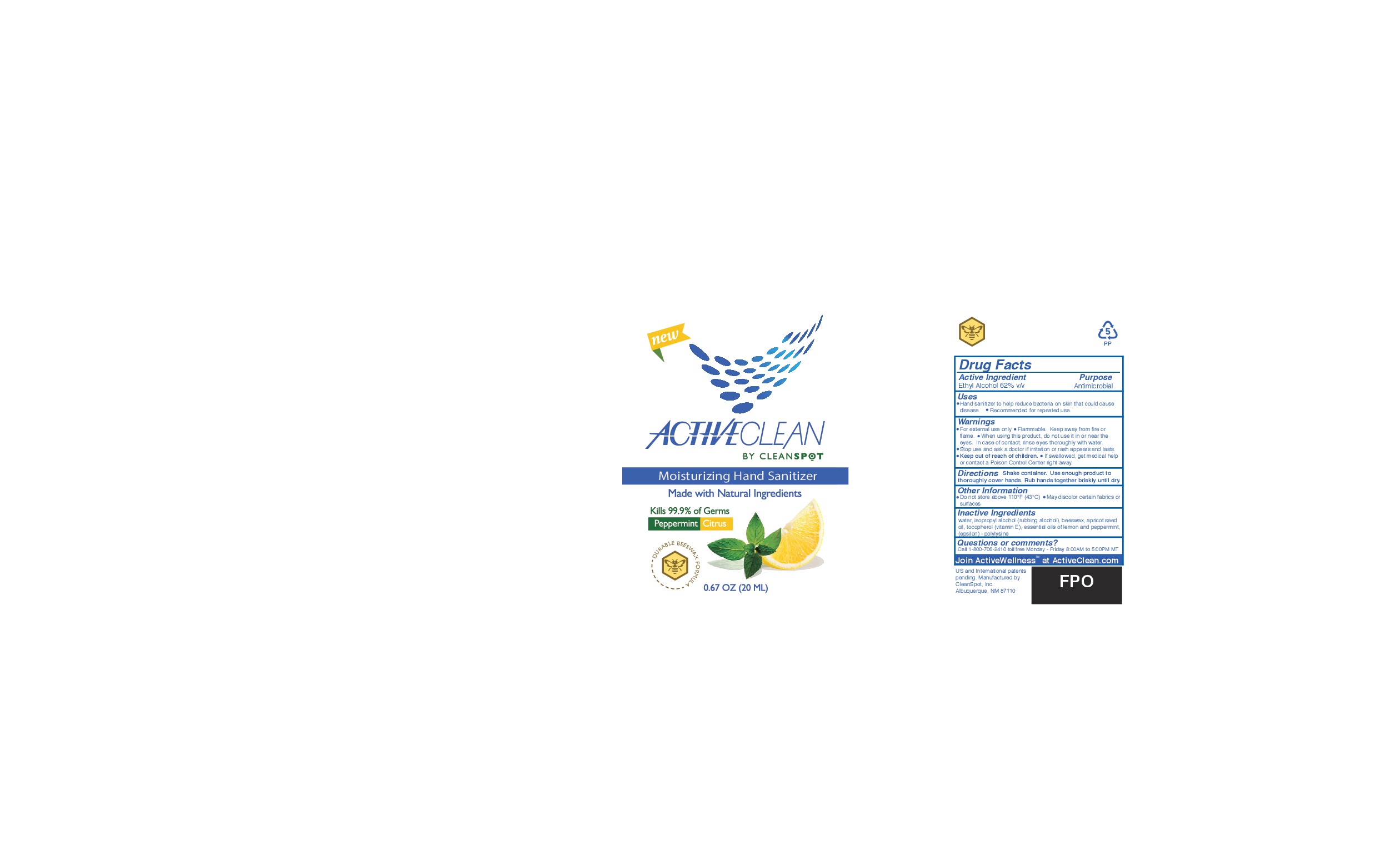 DRUG LABEL: ActiveClean
NDC: 71012-111 | Form: AEROSOL, SPRAY
Manufacturer: CleanSpot, Inc.
Category: otc | Type: HUMAN OTC DRUG LABEL
Date: 20161212

ACTIVE INGREDIENTS: ALCOHOL 62 mL/1 mL
INACTIVE INGREDIENTS: WATER 1 mL/1 mL; .ALPHA.-TOCOPHEROL ACETATE, D- 1 mL/1 mL; APRICOT SEED OIL 1 mL/1 mL; LEMON OIL 1 mL/1 mL; PEPPERMINT OIL 1 mL/1 mL

ActiveClean OTC Spray Hand Sanitizer

DOSAGE AND ADMINISTRATION

Shake container. Use enough product to throughly cover hands. Rub hands together briskly until dry. Children under 6 use only with adult supervision.

WARNINGS

For External Use only. Flammable. Keep away from fire or flame.When using the product, do not use it in or near the eyes. In case of contact, rinse eyes throughly with water. Stop use and ask a doctor if irritation or rash appears and lasts. If swallowed get medical help or contact a PoisonControl Center right away.

INACTIVE INGREDIENT

water, isopropyl alcohol (rubbing alcohol), beeswax, apricit seed oil, tocopherol (Vitamin E), essential oils of lemon and peppermint,(epsilon) - polylysine

PURPOSE

Antimicrobial

ACTIVE INGREDIENT

Ethanol 62% v/v

Keep out of reach of children.

INDICATIONS AND USAGE

- Hand sanitizer to help reduce bacteria on skin that could cause disease
- Recommended for repeated use